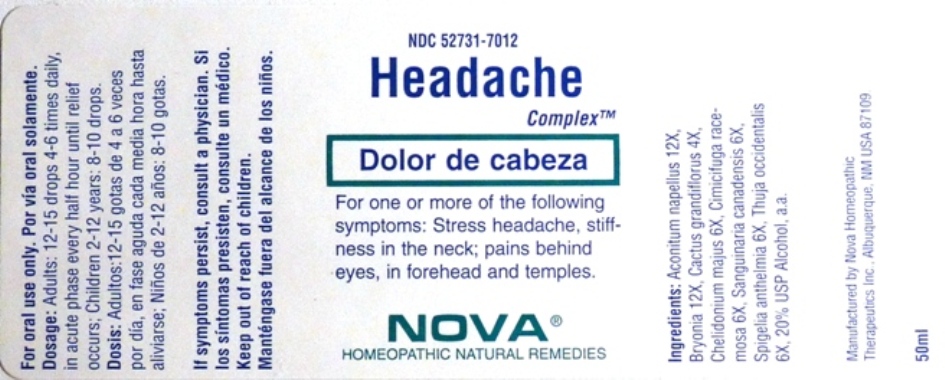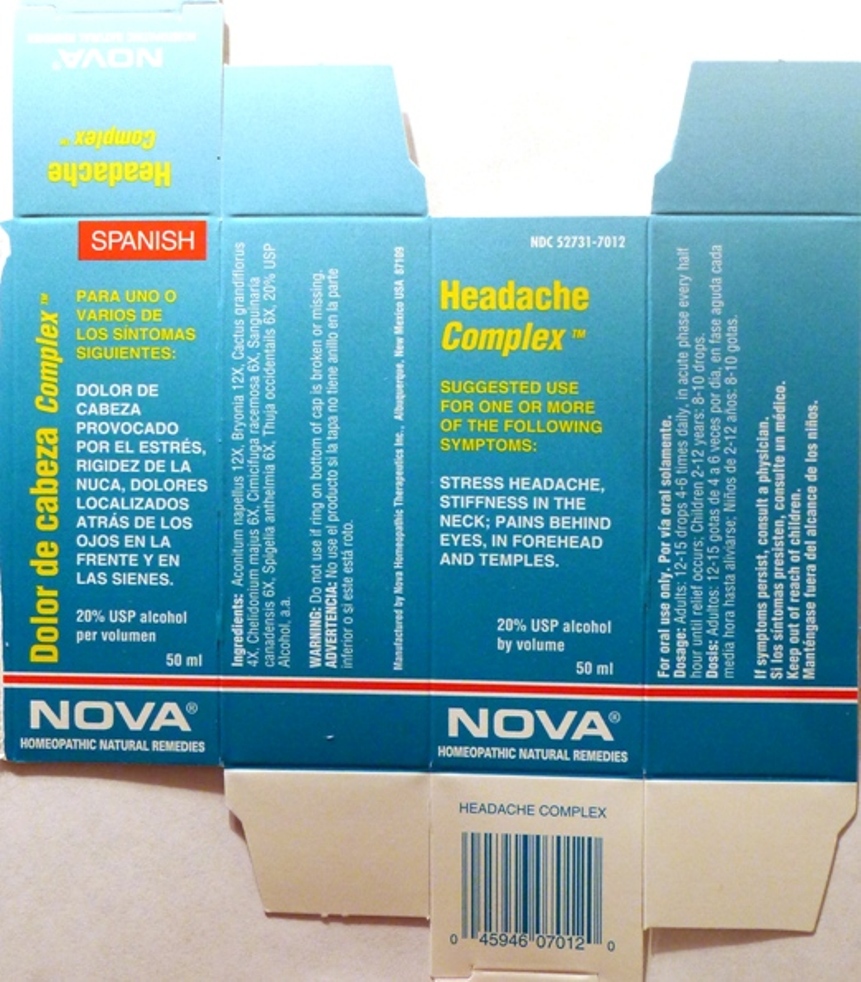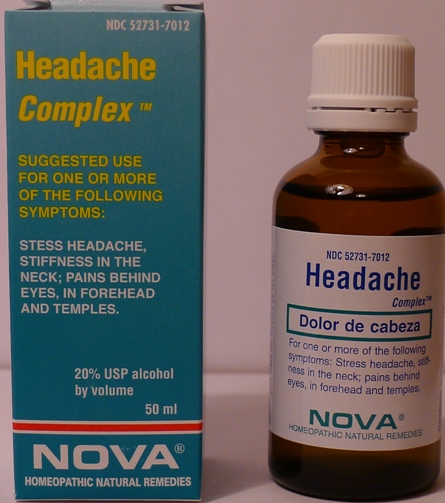 DRUG LABEL: Headache Complex
NDC: 52731-7012 | Form: LIQUID
Manufacturer: Nova Homeopathic Therapeutics, Inc.
Category: homeopathic | Type: HUMAN OTC DRUG LABEL
Date: 20110601

ACTIVE INGREDIENTS: ACONITUM NAPELLUS 12 [hp_X]/1 mL; BRYONIA ALBA ROOT 12 [hp_X]/1 mL; SELENICEREUS GRANDIFLORUS STEM 4 [hp_X]/1 mL; CHELIDONIUM MAJUS 6 [hp_X]/1 mL; BLACK COHOSH 6 [hp_X]/1 mL; SANGUINARIA CANADENSIS ROOT 6 [hp_X]/1 mL; SPIGELIA ANTHELMIA 6 [hp_X]/1 mL; THUJA OCCIDENTALIS LEAFY TWIG 6 [hp_X]/1 mL
INACTIVE INGREDIENTS: ALCOHOL

Headache Complex

Purpose:

Suggested use for one or more of the following symptoms:

Stress headache, stiffness in the neck; pains behind eyes, in forehead and temples.

Usage and Dosage:

For oral use only.

DOSAGE AND ADMINISTRATION

Adults:
In Acute Phase:
12-15 drops, every half hour until relief occurs
When Relief Occurs:
12-15 drops, 4-6 times per day
Children 2-12 years:
8-10 drops, 4-6 times per day

Warnings:

Keep out of reach of children.

WARNINGS

If symptoms persist, consult a physician.
Do not use if ring on bottom of cap is broken or missing.

Active Ingredients:

Aconitum napellus 12X, Bryonia 12X, Cactus grandiflorus 4X, Chelidonium majus 6X, Cimicifuga racemosa 6X, Sanguinaria canadensis 6X, Spigelia anthelmia 6X, Thuja occidentails 6X

Inactive Ingredients:

Alcohol, 20% USP

QUESTIONS

Manufactured by Nova Homeopathic Therapeutics Inc., Albuquerque, New Mexico USA 87109
1-800-225-8094

PACKAGE LABEL

Headache Complex Product

Headache Complex Bottle Label

Headache Complex Box